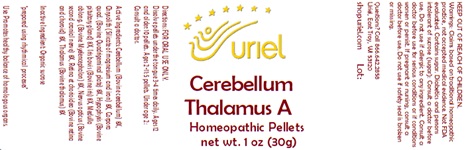 DRUG LABEL: Cerebellum Thalamus A
NDC: 48951-3262 | Form: PELLET
Manufacturer: Uriel Pharmacy Inc.
Category: homeopathic | Type: HUMAN OTC DRUG LABEL
Date: 20240118

ACTIVE INGREDIENTS: BOS TAURUS CEREBELLUM 8 [hp_X]/1 1; SILICON DIOXIDE 8 [hp_X]/1 1; BOS TAURUS BRAIN 8 [hp_X]/1 1; BOS TAURUS PITUITARY GLAND 8 [hp_X]/1 1; BOS TAURUS EYE 8 [hp_X]/1 1; SUS SCROFA THALAMUS 8 [hp_X]/1 1
INACTIVE INGREDIENTS: SUCROSE

Cerebellum Thalamus A

INDICATIONS AND USAGE

Directions: FOR ORAL USE ONLY.

DOSAGE AND ADMINISTRATION

Dissolve pellets under the tongue 3-4 times daily. Ages 12 and older: 10 pellets. Ages 2-11: 5 pellets. Under age 2: Consult a doctor.

ACTIVE INGREDIENT

Active Ingredients: Cerebellum (Bovine cerebellum) 8X, Chrysolith (Silicate of magnesium and iron) 8X, Corpora quad. (Bovine Quadrigeminal plate) 8X, Hypophysis (Bovine pituitary gland) 8X, Iris bovis (Bovine iris) 8X, Medulla oblong. (Bovine Myelencephalon) 8X, Nervus opticus (Bovine second cranial nerve) 8X, Retina et chorioidea (Bovine retina and choroid) 8X, Thalamus (Bovine thalamus) 8X

Inactive Ingredient: Sucrose

"prepared using rhythmical processes"

PURPOSE

Use: Promotes healthy balance of homologous organs.

KEEP OUT OF REACH OF CHILDREN.

WARNINGS

Warnings: Claims based on traditional homeopathic practice, not accepted medical evidence. Not FDA evaluated. Contains sugar. Diabetics and persons intolerant of sucrose (sugar): Consult a doctor before use. Do not use if allergic to any ingredient. Consult a doctor before use for serious conditions or if conditions worsen or persist. If pregnant or nursing, consult a doctor before use. Do not use if safety seal is broken or missing.

Questions? Call 866.642.2858
Uriel, East Troy WI 53120
shopuriel.com